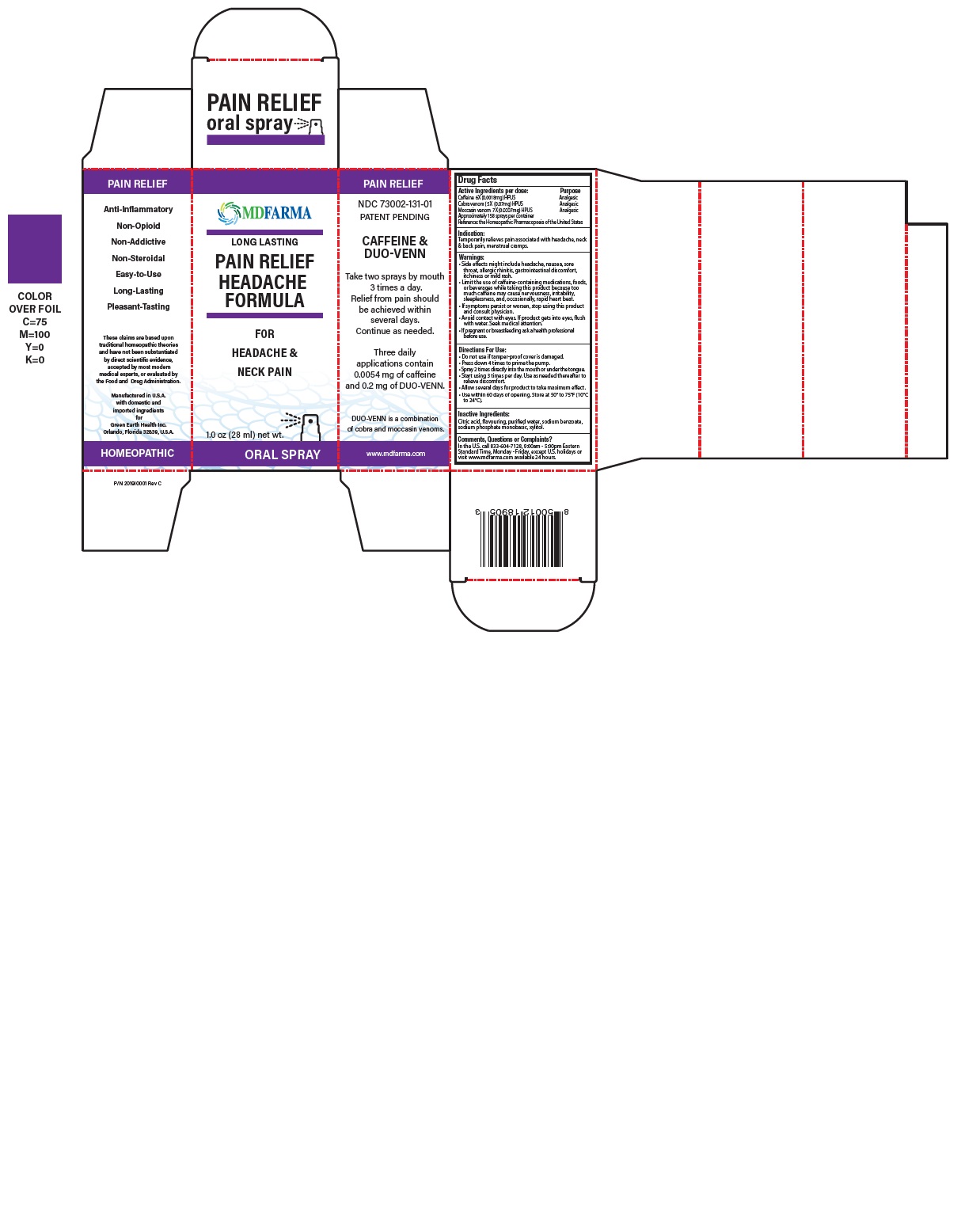 DRUG LABEL: PAIN RELIEF CAFFEINE AND SNAKE VENOM
NDC: 73002-131 | Form: SPRAY
Manufacturer: Green Earth Health Inc.
Category: homeopathic | Type: HUMAN OTC DRUG LABEL
Date: 20250722

ACTIVE INGREDIENTS: CAFFEINE 6 [hp_X]/1 mL; NAJA NAJA VENOM 4 [hp_X]/1 mL; AGKISTRODON PISCIVORUS VENOM 6 [hp_X]/1 mL
INACTIVE INGREDIENTS: ANHYDROUS CITRIC ACID; WATER; SODIUM BENZOATE; SODIUM PHOSPHATE, MONOBASIC, ANHYDROUS; XYLITOL; VANILLA

Drug Facts

Active Ingredients Purpose

Caffeine (Coffeinum) 6X (0.0018mg) HPUS Analgesic
Cobra venom (Naja naja) 5X (0.07mg) HPUS Analgesic
Moccasin venom (A.piscivorus) 7X (0.0007mg) HPUS Analgesic

Approximately 158 sprays per container

Reference: the Homeopathic Pharmacopoeia of the United States (HPUS)

Indication:

Temporarily relieves pain associated with headache, neck and back pain, menstrual cramps

Warnings:

• Side effects might include headache, nausea, sore throat, allergic rhinitis, gastrointestinal discomfort, itchiness or mild rash.
• Limit the use of caffeine-containing medications, foods, or beverages while taking this product because too much caffeine may cause nervousness, irritability, sleeplessness, and, occasionally, rapid heart beat.
• If symptoms persist or worsen, stop using this product and consult physician.
• Avoid contact with eyes. If product gets into eyes, flush with water. Seek medical attention.
• If pregnant or breastfeeding ask a health professional before use.
• Keep out of reach of children.

Directions For Use:

- Do not use if tamper-proof cover is damaged.
- Press down 4 times to prime the pump.
- Spray 2 times directly into the mouth or under the tongue.
- Start using 3 times per day. Use as needed thereafter to relieve discomfort.
- Allow several days for product to take maximum effect.
- Use within 60 days from opening. Store at 50° to 75°F (10°C to 24°C)

Inactive Ingredients:

Citric acid, flavouring, purified water, sodium benzoate, sodium phosphate monobasic, xylitol